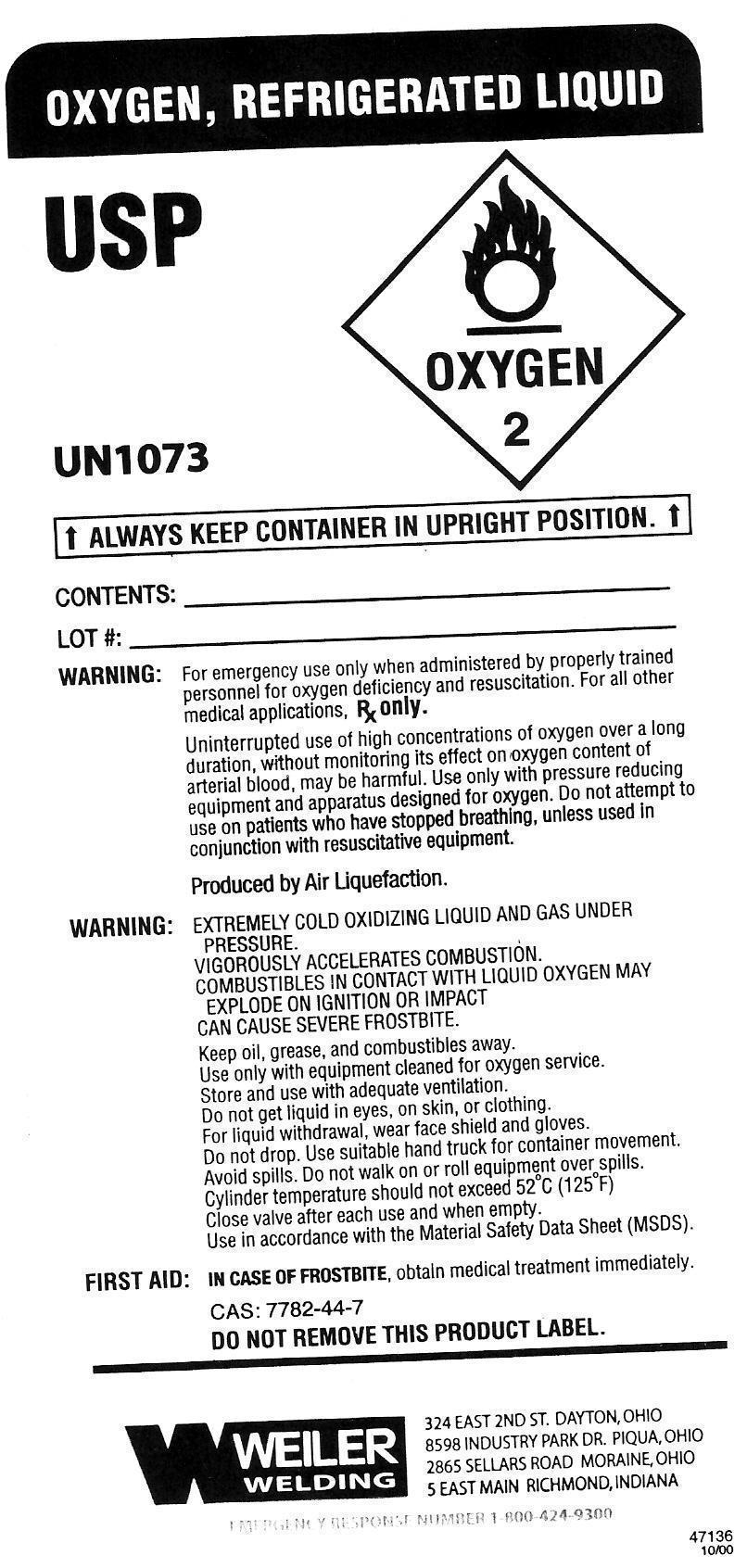 DRUG LABEL: Oxygen
NDC: 48664-001 | Form: LIQUID
Manufacturer: Weiler Welding Company
Category: prescription | Type: HUMAN PRESCRIPTION DRUG LABEL
Date: 20161107

ACTIVE INGREDIENTS: Oxygen 1.13835106 kg/1 L

OXYGEN, REFRIGERATED LIQUID

PACKAGE LABEL

USP
[OXYGEN 2 SYMBOL]
UN1073
ALWAYS KEEP CONTAINER IN UPRIGHT POSITIONCONTENTS: _______________________________________
LOT #: ____________________________________________
WARNING:For emergency use only when administered by properly trained personnel for oxygen deficiency and resuscitation. For all other medical applications, ℞ only. Uninterrupted use of high concentrations of oxygen over a long duration, without monitoring its effect on oxygen content of arterial blood, may be harmful. Use only with pressure reducing equipment and apparatus designed for oxygen. Do not attempt to use on patients who have stopped breathing, unless used in conjunction with resuscitative equipment.
Produced by Air Liquefaction.
WARNING:EXTREMELY COLD OXIDIZING LIQUID AND GAD UNDER PRESSURE.
VIGOROUSLY ACCELERATES COMBUSTION.
COMBUSTIBLES IN CONTACT WITH LIQUID OXYGEN MAY EXPLODE ON IGNITION OR IMPACT.
CAN CAUSE SEVERE FROSTBITE.
Keep oil, grease, and combustibles away.
Use only with equipment cleaned for oxygen service.
Store and use with adequate ventilation.
Do not get liquid in eyes, on skin, or clothing.
For liquid withdrawal, wear face shield and gloves.
Do not drop. Use suitable hand truck for container movement.
Avoid spills. Do not walk on or roll equipment over spills.
Cylinder temperature should not exceed 52 degrees C (125 degrees F)
Close valve after each use and when empty.
Use in accordance with the Material Safety Data Sheet (MSDS).
FIRST AID: IN CASE OF FROSTBITE, obtain medical treatment immediately.
CAS: 7782-44-7
DO NOT REMOVE THIS PRODUCT LABEL.
[Weiler Welding Logo]
2400 SANDRIDGE DR. DAYTON, OHIO
8598 INDUSTRY PARK DR. PIQUA, OHIO
2865 SELLARS ROAD MORAINE, OHIO
5 EAST MAIN RICHMOND, INDIANA
EMERGENCY RESPONSE NUMBER: 1-800-424-9300